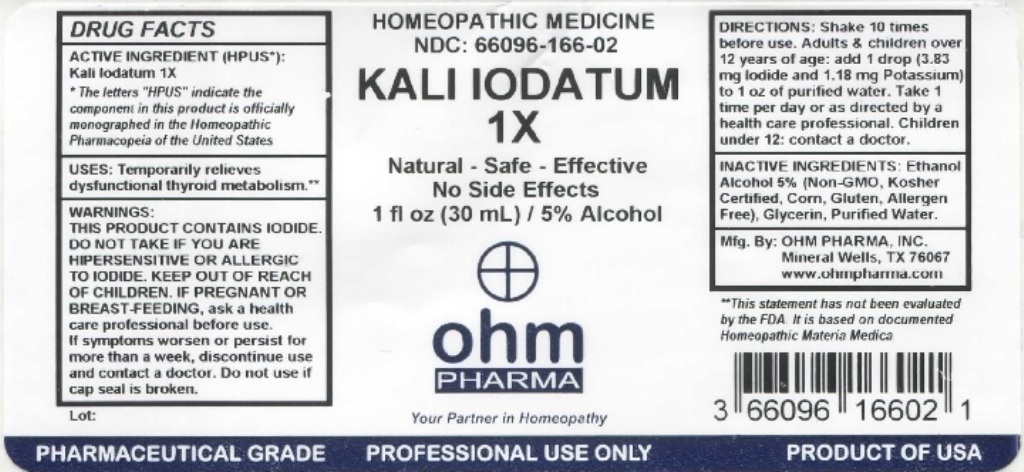 DRUG LABEL: Kali Iodatum 1X
NDC: 66096-166 | Form: LIQUID
Manufacturer: OHM PHARMA INC.
Category: homeopathic | Type: HUMAN OTC DRUG LABEL
Date: 20211229

ACTIVE INGREDIENTS: POTASSIUM IODIDE 1 [hp_X]/30 mL
INACTIVE INGREDIENTS: ALCOHOL; GLYCERIN; WATER

OHM Kali Iodatum 1X

ACTIVE INGREDIENT (HPUS*): Kali Iodatum 1X.

* The letters "HPUS" indicate that the component in this product is officially monographed in the Homeopathic Pharmacopeia of the United States.

INDICATIONS AND USAGE

USES: Temporarily relieves dysfunctional thyroid metabolism.**

**This statement has not been evaluated by the FDA. It is based on documented Homeopathic Materia Medica.

WARNINGS

WARNINGS: THIS PRODUCT CONTAINS IODIDE. DO NOT TAKE IF YOU ARE HIPERSENSITIVE OR ALLERGIC TO IODIDE. IF YOU ARE PREGNANT OR BREAST-FEEDING,ask a health care professional before use. If symptoms worsen or persist for more than a week, discontinue use and contact a doctor.

- Keep out of reach of children.

DOSAGE AND ADMINISTRATION

DIRECTIONS: Shake 10 times before use. Adults & children over 12 years of age: add 1 drop (3.83 mg iodide and 1.18 mg Potassium) to 1 oz of purified water. Take 1 times per day or as directed by a health care professional. Children under 12: contact a doctor.

Do not use if cap seal is broken.

INACTIVE INGREDIENT

INACTIVE INGREDIENTS: Ethanol Alcohol 5% (Non-GMO, Kosher Certified, Corn, Gluten Allergen Free), Glycerin, Purified Water.

QUESTIONS

Mfg. By: OHM Pharma, INC. Mineral Wells, TX 76067

www.ohmpharma.com

PACKAGE LABEL

HOMEOPATHIC MEDICINE

NDC: 66096-166-02

KALI IODATUM 1X

Natural - Safe - Effective

No Side Effects

1 fl oz (30mL) / 5% Alcohol

PRODUCT OF USA

PURPOSE

Temporarily relieves dysfunctional thyroid metabolism.